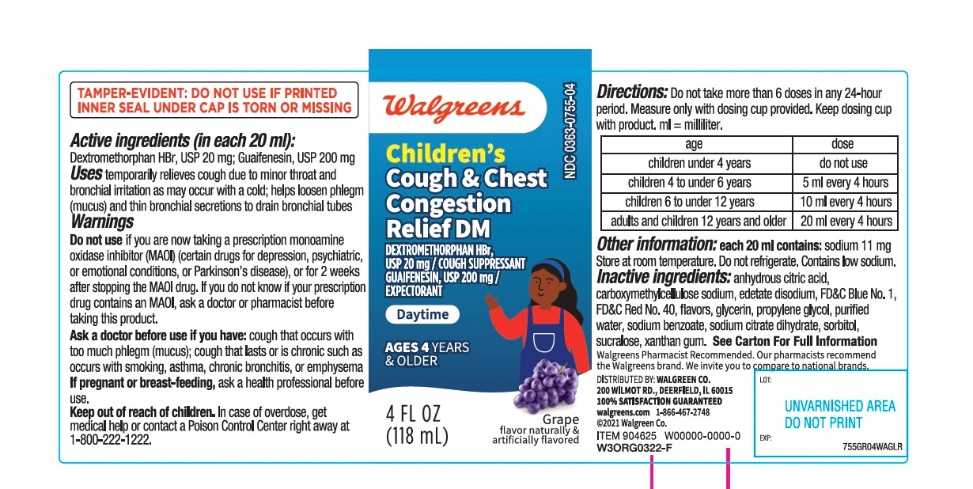 DRUG LABEL: Walgreens Daytime

NDC: 0363-7550 | Form: LIQUID
Manufacturer: WALGREENS CO.
Category: otc | Type: HUMAN OTC DRUG LABEL
Date: 20251201

ACTIVE INGREDIENTS: DEXTROMETHORPHAN HYDROBROMIDE 5 mg/5 mL; GUAIFENESIN 100 mg/5 mL
INACTIVE INGREDIENTS: ANHYDROUS CITRIC ACID; EDETATE DISODIUM; FD&C BLUE NO. 1; FD&C RED NO. 40; POTASSIUM CITRATE; PROPYLENE GLYCOL; WATER; SODIUM BENZOATE; SORBITOL; SUCRALOSE; XANTHAN GUM

Walgreens Children’s Cough and Chest Congestion

Active ingredients (in each 5 mL)

Dextromethorphan HBr USP 5 mg

Guaifenesin. USP 100 mg

Purposes for Day Time

Cough suppressant

Expectorant

Uses

- temporarily relieves cough due to minor throat and bronchial irritation as may occur with a cold
- helps loosen phlegm (mucus) and thin bronchial secretions to drain bronchial tubes

Warnings

Do not us

- If you are now taking a prescription monoamine oxidase inhibitor (MAOI) (certain drugs for depression, psychiatric or emotional conditions, or Parkinson's disease), or for 2 weeks after stopping the MAOI drug. If you do not know if your prescription drug contains an MAOI, ask a doctor or pharmacist before taking this product.

Ask a doctor before use if you have

- cough that occurs with too much phlegm (mucus)
- cough that lasts or is chronic such as occurs with smoking, asthma, chronic bronchitis or emphysema

Stop use and ask a doctor if

- cough last more than 7 days, comes back or is accompanied by fever, rash, or persistent headache. These could be signs of a serious condition.

If pregnant or breast-feeding,

ask a health professional before use.

Keep out of reach of children.

In case of overdose, get medical help or contact a Poison Control Center (1-800-222-1222) right away.

Directions

- measure only with dosing cup provided.
- keep dosing cup with product
- mL= milliliter
- do not take more than 6 doses in any 24-hour period

age | dose
Children under 4 years | Do not use
Children 4 to under 6 years | 5 mL every 4 hours
Children 6 to under 12 years | 10 mL every 4 hours
Adults and children 12 years and older | 20 mL every 4 hours

Other information

- each 5 mL contains: sodium 3 mg
- store at room temperature. Do not refrigerate
- contain low sodium
- do not use if printed seal under cap is torn or missing

Inactive ingredients

anhydrous citric acid, edetate disodium, FD&C Blue # 1, FD&C Red # 40, flavor, potassium citrate, propylene glycol, purified water, sodium benzoate, sorbitol, sucralose, xanthan gum

Questions or comments?

1-866-467-2748

Principal Display Panel

NDC# 0363-7550-04

Compare to the Children's Robitussin®Daytime Cough & Chest Congestion DM

Children’s COUGH & CHEST CONGESTIONS

Wal-Tussin®DM

DEXTROMETHORPHAN HBr, USP 5 mg / 5 mL

COUGH SUPPRESSANT

GUAIFENESIN, USP 100 mg / 5 mL

EXPECTORANT

DAYTIME

NON-DROWSY

Relievescough, chest congestion & mucus

4 YEARS & OLDER

GRAPE FLAVOR

NATURALLY AND ARTIFICIALLY FLAVORED

Dosage cup included

2 - 4 FL OZ (118 mL) BOTTLES

Walgreens PHARMACIST RECOMMENDED†

Health expertise you rely on, quality you trust

†Walgreens Pharmacists Survey

*This product is not manufactured or distributed by Pfizer, owner of the registered trademarks Children’s Robitussin®

DISTRIBUTED BY: WALGREEN CO.

200 WILMOT RD., DEERFIELD, IL 60015

Walgreens

100% SATISFACTION GUARANTEED

Walgreens.com ©2018 Walgreen Co.